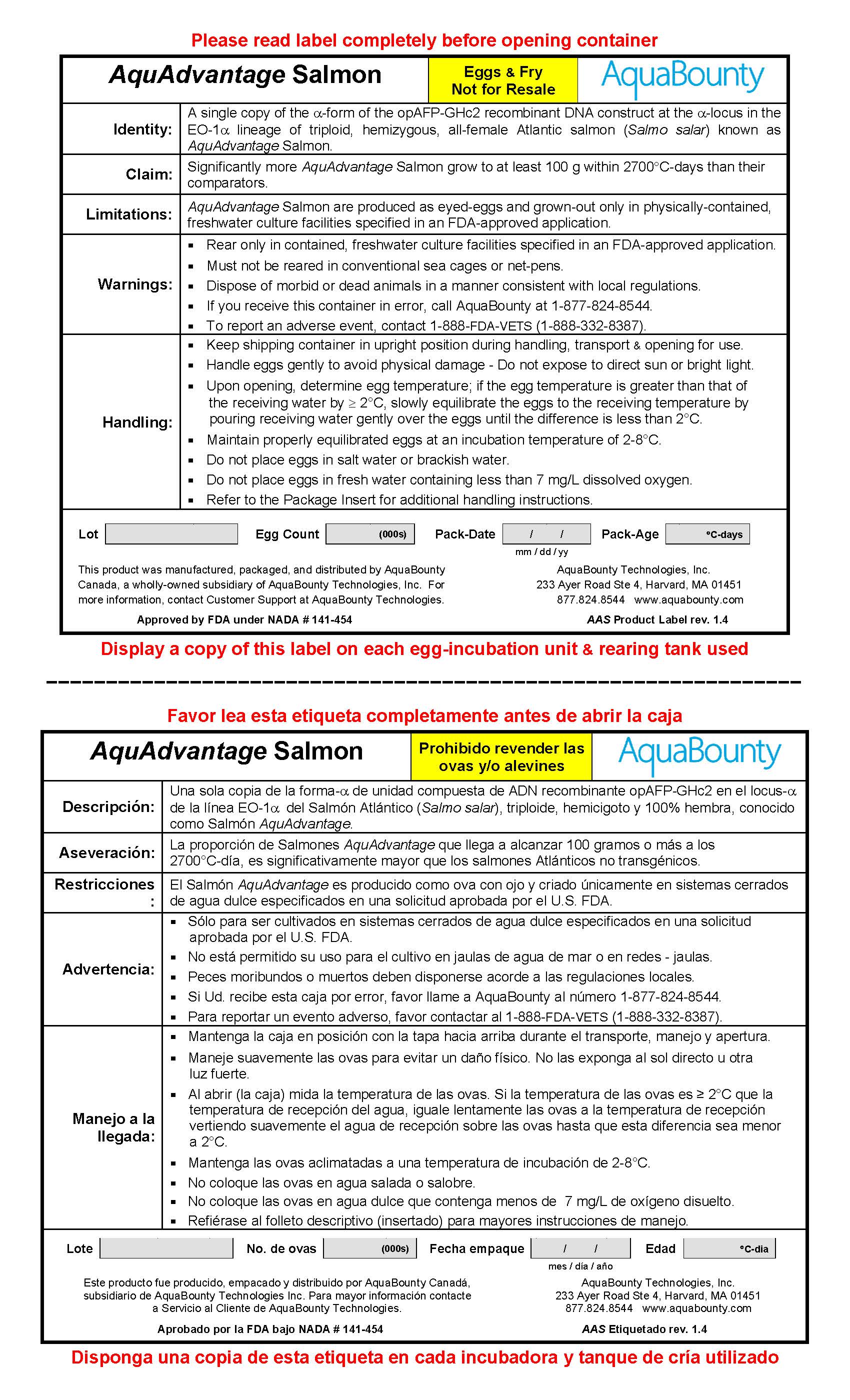 DRUG LABEL: AquAdvantage Salmon
NDC: 86053-001 | Form: NOT APPLICABLE
Manufacturer: AquaBounty Technologies, Inc.
Category: other | Type: INTENTIONAL ANIMAL GENOMIC ALTERATION LABEL
Date: 20241219

ACTIVE INGREDIENTS: ATLANTIC SALMON TRANSGENIC WHOLE (OPAFP-GHC2 RDNA CONSTRUCT INSERTED INTO .ALPHA.-LOCUS IN THE EO-1.ALPHA. LINEAGE) 1 [Amb'a'1'U]/1 [Amb'a'1'U]

opAFP-GHc2 rDNA construct in EO-1α lineage Atlantic salmon (AquAdvantage Salmon)

INSTRUCTIONS FOR USE

1. Product Definition

1.1 Identity

A single copy of the -form of the opAFP-GHc2 recombinant DNA construct at the -locus in the EO-1 lineage of triploid, hemizygous, all-female Atlantic salmon (Salmo salar) known as AquAdvantage Salmon.

1.2 Claim

Significantly more AquAdvantage Salmon grow to at least 100 g within 2700°C-days than their comparators.

1.3 Limitations

AquAdvantage Salmon are produced as eyed-eggs and grown-out only in physically-contained, freshwater culture facilities specified in an FDA-approved application.

2. Product Use

2.1 Initial Receipt

Remove the exterior cardboard packaging from the shipping container, then clean and disinfect the outside of the interior plastic crate before bringing it into the culture facility. Open the plastic crate in an area that is designated for egg receipt, and remove the eggs for disinfection as described in §2.2. Dispose of all packaging and the empty egg trays according to local regulations.

2.2 Handling & Disinfection

Important:This product was disinfected prior to packaging for shipment. If egg hatch has initiated during transit, do not subject to further disinfection as described below.

Open the plastic crate and determine the temperature of the eggs in the top and bottom trays. If the egg temperature is greater than that of the receiving water by 2°C, slowly equilbrate the eggs to the receiving temperature by pouring receiving water gently over the eggs until the difference is less than 2°C

Disinfect the eggs in accordance with local regulations; following disinfection, rinse the eggs gently but thoroughly in running water at the receiving temperature before placing them in incubators.

2.3 Incubation & Hatch

In a vertically-stacked Heath type incubator system, stock no more than 10,000 eggs in a single tray, preferably in a single layer. Adjust water flow to ~10 L/min and maintain egg-incubation temperature at ~6-8°C.* Clean the individual trays, removing dead eggs, a minimum of twice per week. Following hatch, use a substrate when alevin become more active, typically at ~20% yolk sac absorption.

* Eggs may be incubated at water temperatures lower than the range stated for the purpose of delaying hatch.

2.4 First-Feeding & Initial Culture

Before yolk sac absorption is complete, transfer the alevin to tanks appropriate for 1st-feeding and gradually increase water temperature to a maximum of ~15-16°C. When the yolk sac is fully absorbed, increase water flow rate to ~20 L/min. AquAdvantage Salmon grow very rapidly at this life stage. For maximum growth performance: it is recommended to use freshwater flow-through, rather than recirculation, until they are feeding well; increase the number of hours of light to 24 hours in a period of 5 7 days; and, feed to satiety at least once per hour using a manual and automated feeding system and appropriate pellet size, which will change several times during the first 2-3 months. If capabilities do not allow for optimum conditions, feed fry to satiety a minimum of six times, and preferably once per hour, during operational day-length. In either scenario, flushexcess feed from tanks once a day.

Observe fry carefully during this period for any change in behavior, which could indicate a deterioration of culture conditions that might lead to unnecessary mortality. It is recommended to grade these fish as needed; taking into account the accelerated growth of these fish.

2.5 Grow-Out & Processing

Transfer fry to larger tanks for grow-out at a body weight consistent with established practices. To optimize growth performance, maintain dissolved oxygen content at a minimum value of 7 mg/L and stocking density at a value less than the maximum sustainable under local culture conditions. Feed fish to satiety a minimum of twice per day according to manufacturers guidelines using a high-fat commercial diet of appropriate pellet-size; automatic feeders are recommended. Important:You must euthanizeAquAdvantage Salmon before they leave the grow-out facility for processing.

3. Conditions of Use

Rear only in contained, freshwater culture facilities specified in an FDA-approved application. Do not grow AquAdvantage Salmon in net pens or release them into the environment. Dispose of dead or morbid fish in a manner consistent with local regulations.

4. Growth Performance

In a controlled study conducted for 2700°C-days after first-feeding, AquAdvantage Salmon and diploid comparators achieved average body weights of 261.0 g and 73.6 g, respectively; the proportion of individual AquAdvantage Salmon with a body weight greater than 100 g was 98.6% compared to 4.9% for the comparators. These differences in average body weight and proportion of fish weighing more than 100 g at 2700°C-days were significant (p < 0.0001).

Growth Performance at 2700°C-days

 | AquAdvantage; Salmon | Comparator Diploid Salmon
Number of Fish | 369 | 369
Mean Weight (g) ± SE | 261.0 ± 3.3 | 72.6 ± 1.0
Weight Range | 16.9 - 426.3 | 11.0 - 118
Fish > 100 g (%) | 364 (98.6) | 15 (4.9)

5. Animal Safety

In a controlled study, some juvenile AquAdvantage Salmon exhibited changes in gross morphology similar in number and severity to those observed in diploid comparator salmon; these changes most often affected the operculum and gill structure, jaw, or fins. The degree of change from a perfectly-formed fish was ranked as none, slight, moderate, or severe; the vast majority of these malformations were regarded as slight. No remarkable differences were observed in the morphology of internal body structures or relative organ weights.

Gross Morphologic Change in Juveniles

 | AquAdvantage; Salmon |  | Comparator; Diploid Salmon
 | (n) | (%) | (n) | (%)
None | 150 | 89.8 | 156 | 83.4
Slight | 12 | 7.2 | 31 | 16.6
Moderate | 4 | 2.4 | 0 | 0
Severe | 1 | 0.6 | 0 | 0
Totals | 167 | 100.0 | 187 | 100.0

Based on a sampling and assessment of three batches of pre-smolt (~20-60 g) fish from the 2010 and 2012 year classes of AquAdvantage Salmon, the following types and rates of gross morphologic irregularities were observed:

 | % Spinal | % Jaw | % Operculum | % Other
Moderate Irregularities | 0 - 4.3 | 0.1 – 1.4 | 0 - 5.6 | 0 - 2.5
Severe Irregularities^1 | 0 - 0.4 | 0 | 0 | 0

^1 Severe irregularities are those which could have a significant impact on viability or render the fish unfit for commercial sale.

Based on data collected on the 2008-2012 year classes of AquAdvantage Salmon, the following tables present reported typical ranges for mortality and morbidity, respectively, on a monthly basis for different life-stages.

Mortality Observed in AquAdvantage Salmon by Life-Stage

on a Monthly Basis^1

Life Stage | Approximate Time Period Post First Feeding in Months | Range of % Mortality on a Monthly Basis
Eggs and Yolk-sac Fry | 0 | 2.2 to 5.1
Fry from First Feeding to 5 g Size | ~1 to 2 | 1.0 to 9.8
Pre-smolt | ~3 to 5 | 0.1 to 4.0
Juveniles | ~6 to 11 | 0.1 to 1.8
Late Juveniles to Adults | ~12 to 24 | 0.2 to 5.2

^1 Non-representative high values due to one-time events or atypical conditions have been excluded.

Morbidity Observed in AquAdvantage Salmon by Life-Stage

on a Monthly Basis^1

Life Stage | Approximate Time Period Post First Feeding in Months | Range of % Morbidity on a Monthly Basis
Eggs and Yolk-sac Fry | 0 | 0
Fry from first feeding to 5 g size | ~1 to 2 | 0 to 0.4
Pre-smolt | ~3 to 5 | 0 to 3.2
Juveniles | ~6 to 11 | 0 to 2.2
Late Juveniles to Adults | ~12 to 24 | 0 to 3.4

^1 Observations made on fish that were eventually discarded, which included moribund fish with actual or presumptive disease conditions, those with gross morphological irregularities, and fish of inappropriate size.

Document and report substantial increases in morbidity, mortality, or incidence of gross morphologic change in AquAdvantage Salmon as soon as possible to Customer Support at AquaBounty Technologies.

Manufactured, packaged & distributed by AquaBounty Canada, Inc., a wholly-owned subsidiary of AquaBounty Technologies, Inc.

Approved by FDA under NADA # 141-454.

For more information, contact:

Customer Support 877-824-8544

AquaBounty Technologies, Inc. www.aquabounty.com

233 Ayer Road Ste 4
Harvard, MA 01451 USA

1. Definición de Producto

1.1 Identidad

Una sola copia de la forma-a de unidad compuesta de ADN recombinante opAFP-GHc2 en el locus-a de la línea EO-1a del Salmón Atlántico (Salmo salar), triploide, hemicigoto y 100% hembra, conocido como Salmón AquAdvantage.

1.2. Aseveración

La proporción de Salmones AquAdvantage que llega a alcanzar 100 gramos o más a los 2700°C-día, es significativamente mayor que los salmones Atlánticos comparables.

1.3. Restricciones

El Salmón AquAdvantage es producido como ova con ojo y criado únicamente en sistemas cerrados de agua dulce especificados en una solicitud aprobada por el U.S. FDA.

2. Uso del Producto

2.1. Recepción Inicial

Remueva el empaque exterior de cartón del contenedor de envío. Luego limpie y desinfecte el exterior del contenedor de plástico antes de ingresarlo a la instalación de cultivo. Abra el contenedor de plástico en un área designada para la recepción de ovas y remueva las ovas para realizar la desinfección descrita en el punto 2.2. Disponga todo el material de empaque y bandejas de ovas vacías acorde a las regulaciones locales.

2.2 Manejo y Desinfección

Importante: Este producto fue desinfectado previo a su empaque para transporte. Si el proceso de eclosión se ha iniciado durante el tránsito, no proceda con la desinfección descrita más abajo.

Abra la caja de plástico y mida la temperatura de las ovas tanto en la bandeja superior como inferior. Si la temperatura de las ovas es 2°C que la temperatura de recepción del agua, iguale lentamente las ovas a la temperatura de recepción, vertiendo suavemente el agua de recepción sobre las ovas hasta que esta diferencia sea menor a 2°C.

Desinfecte las ovas de acuerdo a las regulaciones locales. Después de la desinfección, proceda a lavar las ovas suave pero minuciosamente con agua corriendo a la temperatura de recepción antes de colocarlas en las incubadoras.

2.3 Incubación y Eclosión

Considerando un sistema de incubación vertical, coloque no más de 10.000 ovas por bandeja, preferentemente en una capa. Ajuste el flujo de agua a ~10 L/min y mantenga la temperatura de a ~6-8°C.* Limpie las bandejas individuales, removiendo las ovas muertas, al menos 2 veces por semana. A continuación de la eclosión, use sustratos cuando los alevines estén más activos, típicamente cuando hayan absorbido el ~20% del saco vitelino.

* Las ovas pueden ser incubadas a temperaturas menores a las indicadas con el propósito de retardar la eclosión.

2.4. Primera Alimentación y Cultivo Inicial

Antes de que el saco vitelino se haya absorbido completamente, transfiera los alevines a tanques apropiados para Primera Alimentación y gradualmente incremente la temperatura hasta un máximo de ~15-16°C. Cuando el saco vitelino este completamente absorbido, incremente el flujo de agua a ~20 L/min. El Salmon AquAdvantage crece en forma muy rápida en esta etapa de vida. Para un máximo crecimiento: es recommendable utilice agua dulce con flujo abierto, en vez de recirculación, hasta que estos estén alimentándose adecuadamente. Incremente el numero de horas de luz hasta alcanzar un ciclo de 24 horas luz continua en un periodo de 5 7 dias desde primera alimentracion. Alimente a los peces a mano o utilizando un sistema de alimentacion automatico, Alimente a saciedad utilizando el adecuando tamaño de pellet, el cual cambiará varias veces durante los 2-3 primeros meses. Si las capacidades no permiten óptimas condiciones, alimente los alevines a saciedad un mínimo de 6 veces por día, preferentemente cada hora, durante la jornada diaria de trabajo. Bajo cualquier escenario, descargue de los tanques el exceso de alimento al menos una vez al día.

Durante este periodo, observe los alevines cuidadosamente de tal manera de detectar cambios de comportamiento que pudieran indicar deterioros en las condiciones de cultivo que pueden conllevar mortalidades innecesarias.

Se recomienda graduar acorde a necesidad teniendo en cuenta el crecimiento acelerado de estos peces.

2.5. Engorda y Proceso

Transfiera los alevines a tanques más grandes para su engorde, acorde a prácticas establecidas. Para optimizar el crecimiento mantenga el nivel de oxígeno disuelto en un valor mínimo de 7 mg/L y densidades de cultivo menores a las condiciones máximas de cultivo local sustentable. Alimente a los peces a saciedad, mínimo dos veces al día acorde a las recomendaciones de los proveedores de alimento, usando dietas altas en lípidos, tamaños de pellets adecuados y sistemas de alimentación automáticos. Importante: Los Salmones AquAdvantage deben ser sacrificados antes de salir de las instalaciones de cultivo para ser procesados.

3. Condiciones de Uso

Sólo para ser cultivados en sistemas de agua dulce, especificados en una solicitud aprobada por el U.S. FDA. No cultive los Salmones AquAdvantage en redes - jaulas ni los libere al medio ambiente. Disponga los peces muertos o moribundos acorde a las regulaciones locales.

4. Crecimiento

En un estudio bajo condiciones controladas desarrollado por 2700°C-día después de primera alimentación, los Salmones AquAdvantage y los diploides comparables, obtuvieron un peso de 261.0 g. y 73.6 g. Respectivamente. Además, la proporción de individuos AquAdvantage con un peso superior a 100 g fue de 98.6% en comparación con 4.9% de sus similares no transgénicos. Estas diferencias en promedio de peso y proporción de peces con pesos mayores a 100 g a los 2700°C-día son estadísticamente significativas (p < 0.0001).

Crecimiento a los 2700°C-día

 | Salmón AquAdvantage | Salmón diploide; comparable
Número de Peces | 369 | 306
Peso Promedio (g) ± ES | 261.0 ± 3.3 | 72.6 ± 1.0
Rango de Peso | 16.9 - 426.3 | 11.0 - 118.0
Peces >100 g (%) | 364 (98.6) | 15 (4.9)

5. Seguridad Animal

En un estudio controlado, algunos juveniles de Salmón AquAdvantage presentaron cambios morfológicos similares en número y severidad a los observados en salmones diploides no transgénicos: estos cambios en la mayoría de los casos afectaron a los opérculos, branquias, mandíbula o aletas. El grado de cambio morfológico puede variar entre no existente, ligero, moderado o severo. En el caso de los Salmones AquAdvantage es considerado como leve. No se observaron diferencias marcadas en la morfología interna o peso relativo de órganos.

Cambios Morfológicos Generales en Juveniles

 | Salmón AquAdvantage |  | Salmón diploide; comparable
 | (n) | (%) | (n) | (%)
Ninguno | 150 | 89.8 | 156 | 83.4
Leve | 12 | 7.2 | 31 | 16.6
Moderado | 4 | 2.4 | 0 | 0
Severo | 1 | 0.6 | 0 | 0
Totales | 167 | 100.0 | 187 | 100.0

Basado en muestreos y evaluaciones de tres grupos de peces pre-smolt (~20-60 g) de las generaciones de los anos 2010 y 2012 del Salmón AquAdvantage, se observaron los siguientes tipos y porcentajes de evidentes irregularidades morfológicas:

 | %; Columna vertebral | % Mandibula | % Operculo | %; Otros
Irregularidades Moderadas | 0 - 4.3 | 0.1 – 1.4 | 0 - 5.6 | 0 - 2.5
Irregularidades Severas^1 | 0 - 0.4 | 0 | 0 | 0

^1 Irregularidades severas son aquellas que pueden tener un impacto significativo sobre la viabilidad o valor comercial de los peces.

Las siguientes tablas - basadas en los datos recogidos de las generaciones de los anos 2008-2012 del Salmón AquAdvantage -presentan los rangos típicos mensuales de mortalidad y morbididad observadas en las diferentes etapas de vida.

Mortalidad Mensual, por Etapa de Vida,

Observada en el Salmón AquAdvantage^1

Etapa de Vida | Periodo de Tiempo Aproximado (en meses) Despues de Primera Alimentacion | Rango de Mortalidad por Mes (%)
Ovas y Alevines de Saco | 0 | 2.2 - 5.1
Alevines – desde Primera Alimentación hasta 5 g | ~1 - 2 | 1.0 - 9.8
Pre-smolt | ~3 - 5 | 0.1 - 4.0
Juveniles | ~6 - 11 | 0.1 - 1.8
Pre-adulto hasta Adulto | ~12 - 24 | 0.2 - 5.2

1 Valores altos no-representativos resultando de eventos singulares o condiciones atipicas han sido excluidos.

Morbididad Mensual, por Etapa de Vida,

Observada en el Salmón AquAdvantage^1

Etapa de Vida | Periodo de Tiempo Aproximado (en meses) Despues de Primera Alimentacion | Rango de Mortalidad por Mes (%)
Ovas y alevines de saco | 0 | 0
Alevines – desde Primera Alimentación hasta 5 g | ~1 - 2 | 0 – 0.4
Pre-smolt | ~3 - 5 | 0 – 3.2
Juveniles | ~6 -11 | 0 – 2.2
Pre-adulto hasta Adulto | ~12 - 24 | 0 – 3.4

^1 Observaciones realizadas en peces que luego fueron eventualmente descartados, incluyendo peces moribundos con signos evidentes o presuntos de enfermedad, peces con reales irregularidades morfologicas y peces de un tamano inapropriado.

Registre y reporte incrementos sustanciales de morbilidad, mortalidad o incidencia de cambios morfológicos generales en los Salmones AquAdvantage tan pronto como sea posible a Servicios al Cliente de AquaBounty Technologies.

Producido, empacado y distribuido por AquaBounty Canadá, subsidiario de AquaBounty Technologies Inc.

Aprobado por la FDA bajo NADA # 141-454.

Para mayor información contacte a:

Servicio al Cliente 877-824-8544

AquaBounty Technologies, Inc. www.aquabounty.com

233 Ayer Road Ste 4
Harvard, MA 01451 USA